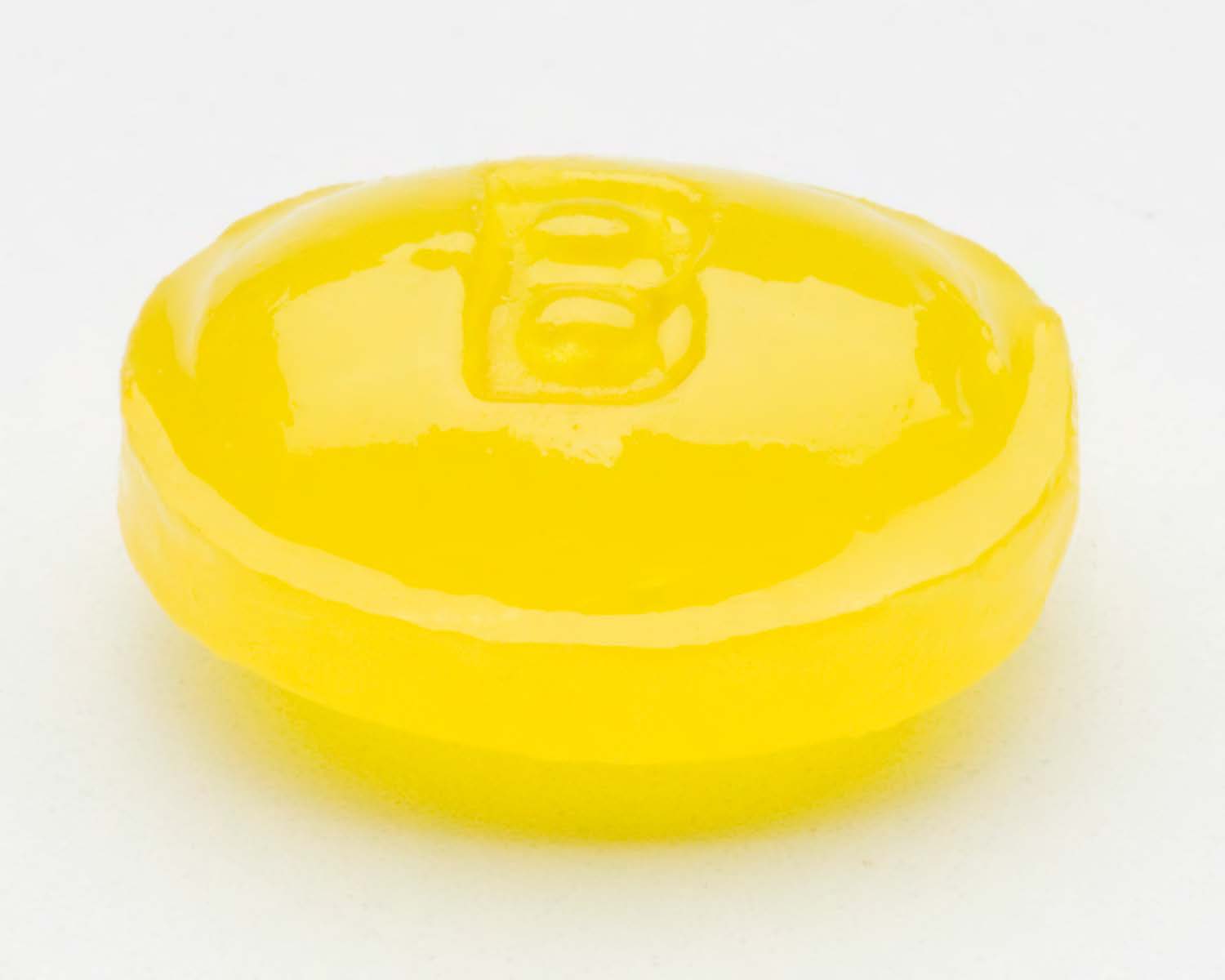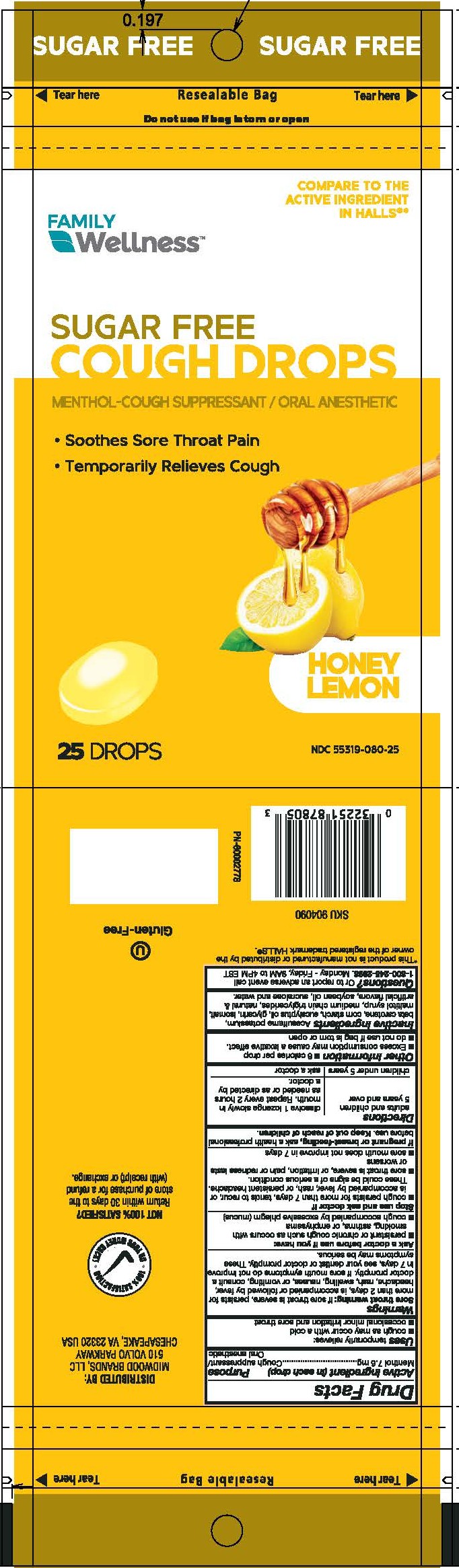 DRUG LABEL: Family Wellness SF Honey Lemon Cough Drops
NDC: 55319-080 | Form: LOZENGE
Manufacturer: Family Dollar
Category: otc | Type: HUMAN OTC DRUG LABEL
Date: 20260224

ACTIVE INGREDIENTS: MENTHOL 7.6 mg/1 1
INACTIVE INGREDIENTS: WATER

Menthol 7.6 mg

Active ingredient (in each drop)

Menthol 7.6 mg

Purpose

Cough suppressant/Oral anesthetic

INDICATIONS AND USAGE

Uses temporarily relieves:

- cough as may occur with a cold
- occasional minor irritation and sore throat

Warnings

Sore throat warning: if sore throat is severe, persists for more than 2 days, is accompanied or followed by fever, headache, rash, swelling, nausea, or vomiting, consult a doctor promptly. If sore mouth symptoms do not improve in 7 days, see your dentist or doctor promptly. These symptoms may be serious.

Ask a doctor before use if you have:

- persistent or chronic cough such as occurs with smoking, asthma, or emphysema
- cough accompanied by excessive phlegm (mucus)

Stop use and ask doctor if

- cough persists for more than 7 days, tends to recur, or is accompanied by fever, rash, or persistent headache. These could be signs of a serious condition.
- sore throat is severe, or irritation, pain or redness lasts or worsens
- sore mouth does not improve in 7 days

PREGNANCY OR BREAST FEEDING

If pregnant or breast-feeding, ask a health professional before use.

Keep out of reach of children.

Directions

adults and children 5 years and over - dissolve 1 lozenge slowly in mouth. Repeat every 2 hours as needed or as directed by a doctor.

children under 5 years - ask a doctor

Other information

- 6 calories per drop
- Excess consumption may cause a laxative effect.
- do not use if bag is torn or open

INACTIVE INGREDIENT

Inactive ingredients: Acesulfame potassium, beta carotene, corn starch, eucalyptus oil, glycerin, isomalt, maltitol syrup, medium chain triglycerides, natural & artificial flavors, soybean oil, sucralose and water.

QUESTIONS

Questions? Or to report an adverse event call 1-800-245-2898. Monday - Friday, 9AM to 4PM EST